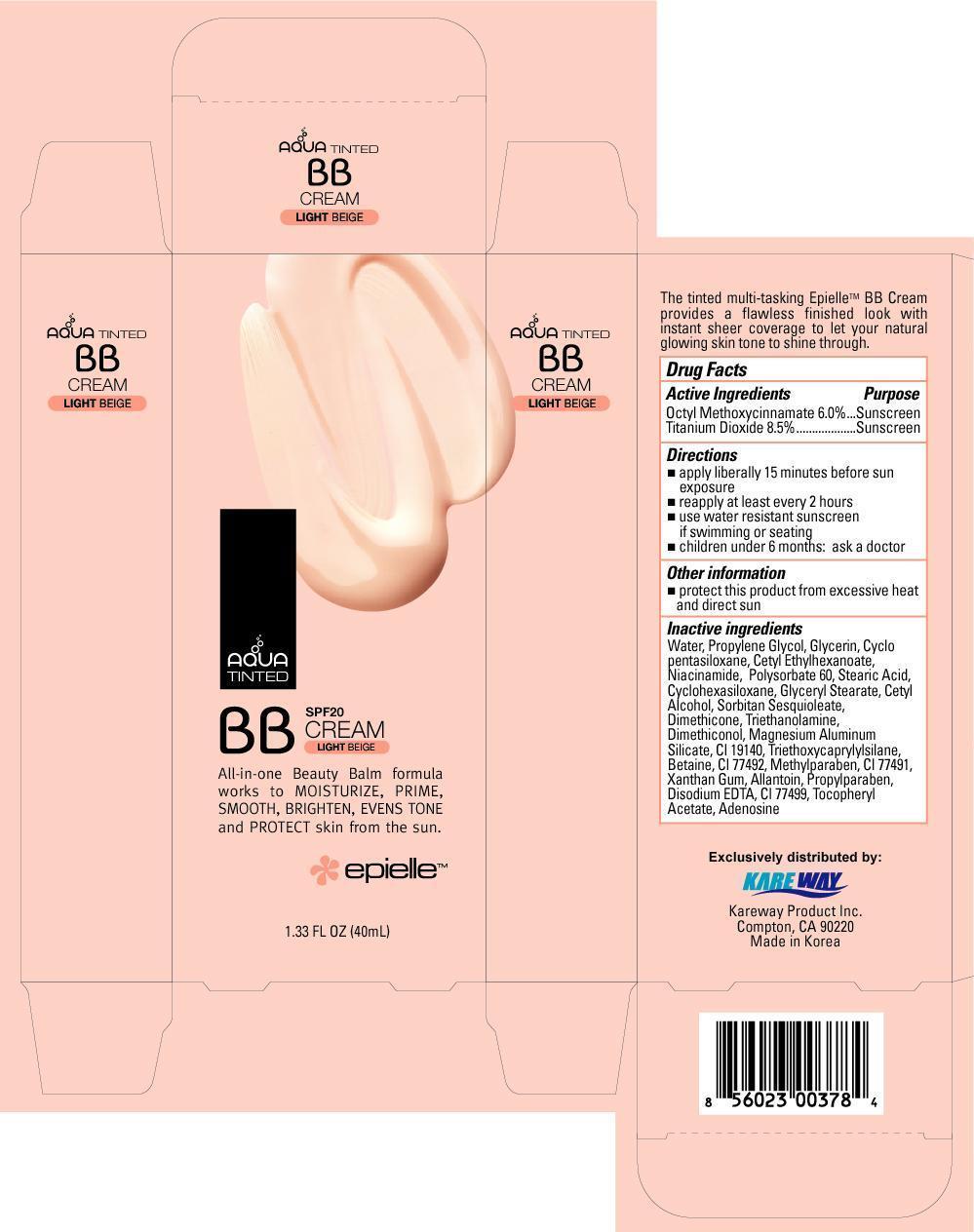 DRUG LABEL: Tinted BB
NDC: 67510-0378 | Form: CREAM
Manufacturer: Kareway Product, Inc.
Category: otc | Type: HUMAN OTC DRUG LABEL
Date: 20171227

ACTIVE INGREDIENTS: OCTINOXATE 6 mg/100 mg; TITANIUM DIOXIDE 8.5 mg/100 mg
INACTIVE INGREDIENTS: WATER; PROPYLENE GLYCOL; GLYCERIN; CETYL ETHYLHEXANOATE; NIACINAMIDE; POLYSORBATE 60; STEARIC ACID; CETYL ALCOHOL; SORBITAN SESQUIOLEATE; DIMETHICONE; MAGNESIUM ALUMINUM SILICATE; BETAINE; METHYLPARABEN; XANTHAN GUM; ALLANTOIN; PROPYLPARABEN; DISODIUM EDTA-COPPER; ADENOSINE

Drug Facts

Active Ingredients

Octyl Methoxycinnamate 6%

Titanium Dioxide 8.5%

Purpose

Sunscreen

Sunscreen

Use

helps prevent sunburn

Warnings

Skin Cancer/Skin Aging Alert: Spending time in the sun increases your risk of skin cancer and early skin aging. This product has been shown only to prevent sunburn, not skin cancer or early skin aging.

For external use only

Do not use

on damaged or broken skin

When using this product

Keep out of eyes. Rinse with water to remove.

Stop use and ask a doctor

if rash occurs

Keep out of reach of children.

If product is swallowed, get medical help or call a Poison Control Center right away.

Directions

- apply liberally 15 minutes before sun exposure
- reapply at least every 2 hours
- use water resistant sunscreen if swimming or seating
- children under 6 months: ask a doctor

Other information

- protect this product from excessive heat and direct sun

Inactive Ingredients

water, proylene glycol, glycerin, cyclo pentasiloxane, cetyl ethylhexanoate, niacinamide, polysorbate 60, stearic acide, cyclohexasiloxane, glyceryl stearate, cetyl alcohol, sorbitan sesquioleate, dimethicone, triethanolamine, dimethiconol, magnesium aluminum silicate, cl 19140, triethoxycaprylylsilane, betaine, cl 77492, methyparaben, cl 77491, xanthan gum, allantoin, propylparaben, disodium EDTA, cl 77499, tocopheryl acetate, adenosine,

Package label

BB Cream